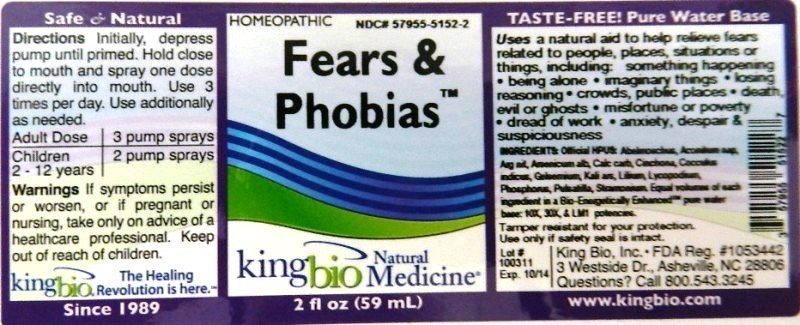 DRUG LABEL: Fears and Phobias
NDC: 57955-5152 | Form: LIQUID
Manufacturer: King Bio Inc.
Category: homeopathic | Type: HUMAN OTC DRUG LABEL
Date: 20120413

ACTIVE INGREDIENTS: ABELMOSCHUS MOSCHATUS SEED 10 [hp_X]/59 mL; ACONITUM NAPELLUS 10 [hp_X]/59 mL; SILVER NITRATE 10 [hp_X]/59 mL; ARSENIC TRIOXIDE 10 [hp_X]/59 mL; OYSTER SHELL CALCIUM CARBONATE, CRUDE 10 [hp_X]/59 mL; CINCHONA OFFICINALIS BARK 10 [hp_X]/59 mL; ANAMIRTA COCCULUS SEED 10 [hp_X]/59 mL; GELSEMIUM SEMPERVIRENS ROOT 10 [hp_X]/59 mL; POTASSIUM ARSENITE ANHYDROUS 10 [hp_X]/59 mL; LILIUM LANCIFOLIUM WHOLE FLOWERING 10 [hp_X]/59 mL; LYCOPODIUM CLAVATUM SPORE 10 [hp_X]/59 mL; PHOSPHORUS 10 [hp_X]/59 mL; PULSATILLA VULGARIS 10 [hp_X]/59 mL; DATURA STRAMONIUM 10 [hp_X]/59 mL
INACTIVE INGREDIENTS: WATER

Fears and Phobias

Active Ingredients

Official HPUS: Abelmoschus, Aconitum napellus, Argentum nitricum, Arsenicum album, Calcarea carbonica, Cinchona officinalis, Cocculus indicus, Gelsemium sempervirens, Kali arsenicosum, Lilium tigrinum, Lycopodium clavatum, Phosphorus, Pulsatilla and Stramonium.

Reference image fears and phobeas.jpg

Inactive Ingredient

Equal volumes of each ingredient in a Bio-Energetically Enhanced pure water base, 10X, 30X and LM1 potencies.

Reference image fears and phobias.jpg

Purpose

Uses a natural aid to help relieve fears related to people, places, situations or things, including:

- something happening
- being alone
- imaginary things
- losing reasoning
- crowds, public places
- death, evil or ghosts
- misfortune or poverty
- dread of work
- anxiety, despair and suspiciousness

Reference image fears and phobias.jpg

Dosage and Administration

Directions: Initially, depress pump until primed. Hold close to mouth and spray one dose directly into mouth. Use 3 times per day. Use additionally as needed.

Adult Dose 3 pump sprays

Children 2-12 years 2 pump sprays

Reference image fears and phobias.jpg

Warnings

If symptoms persist or worsen, or if pregnant or nursing, take only on advice of a healthcare professional.

Other Information: Tamper resistant for your protection. Use only if safety seal is intact.

Reference image fears and phobias.jpg

Keep out of reach of children.

Reference image fears and phobias.jpg

Indications and Usage

Uses a natural aid to help relieve fears related to people, places, situations or things, including: something happening, being alone, imaginary things, losing reasoning, crowds, public places, death, evil or ghosts, misfortune or poverty, dread of work, anxiety, despair and suspiciousness.

Reference image fears and phobias.jpg

PACKAGE LABEL

King Bio Inc.
3 Westside Drive
Asheville, NC 28806
Questions? Call 800.543.3245
www.kingbio.com
Reference image fears and phobias.jpg